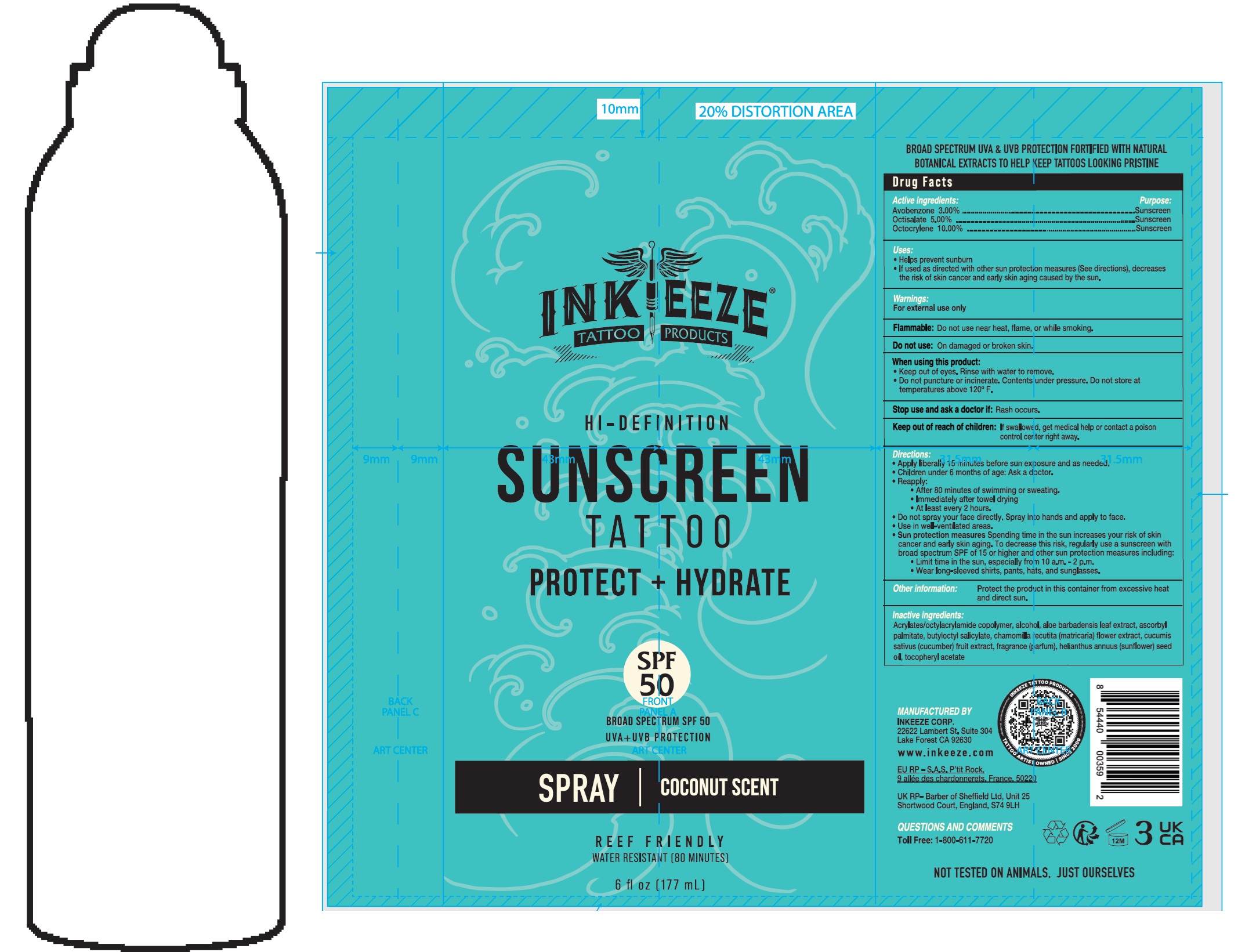 DRUG LABEL: Inkeeze Tattoo Products Hi-Definition Tattoo Sunscreen SPF 50 Coconut Scent
NDC: 87440-901 | Form: LIQUID
Manufacturer: Ink-eeze
Category: otc | Type: HUMAN OTC DRUG LABEL
Date: 20260219

ACTIVE INGREDIENTS: AVOBENZONE 30 mg/1 mL; OCTISALATE 50 mg/1 mL; OCTOCRYLENE 100 mg/1 mL
INACTIVE INGREDIENTS: ALCOHOL; ALOE VERA LEAF; ASCORBYL PALMITATE; BUTYLOCTYL SALICYLATE; CHAMOMILE; CUCUMBER; SUNFLOWER OIL; .ALPHA.-TOCOPHEROL ACETATE

Inkeeze Tattoo Products Hi-Definition Tattoo Sunscreen SPF 50 Coconut Scent

Active ingredients:

Avobenzone 3.00%

Octisalate 5.00%

Octocrylene 10.00%

Purpose:

Sunscreen

Uses:

- Helps prevent surburn
- If used as directed with other sun protection measures (See directions), decreases the risk of skin cancer and early skin aging caused by the sun.

Wrnings:

For external use only

Flammable:Do not use near heat, flame, or while smoking.

Do not use:

On damaged or broken skin.

When using this product:

- Keep out of eyes. Rinse with water to bremove.
- Do not puncture or incinerate. Contents under pressure. Do not store at temperatures above 120° F.

Stop use and ask a doctor if:

Rash occurs.

Keep out of reach of children.

If swallowed,get medical help or contact a poison control center right away.

Directions:

- Apply liberaliy 15 minutes before sun exposure and as needed.
- Children under 6 months of age: Ask a doctor.
- Reapply:
- After 80 minutes of swimming or sweating.
- Immediately after towel drying
- At least every 2 hours.
- Do not spray your face directly. Spray into hands and apply to face.
- Use in well-ventilated areas.
- Sun protection measures. Spending time in the sun increases your risk of skin cancer and early skin aging. To decrease this risk, regularly use a sunscreen with broad spectrum SPF of 15 or higher and other sun protection measures including:
- Limit time in the sun, especially from 10 a.m. - 2 p.m.
- Wear long-sleeved shirts, pants, hats, and sunglasses.

Other information:

Protect the product in this container from excessive heat and direct sun.

Inactive ingredients:

Acrylates/octylacrylamide copolymer, alcohol, aloe barbadensis leaf extract, ascorbyl palmitate, butyloctyl salicylate, chamomilla recutita (matricaria) flower extract, cucumis sativus (cucumber) fruit extract, fragrance (parfum), helianthus annuus (sunflower) seed oil, tocopheryl acetate